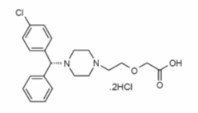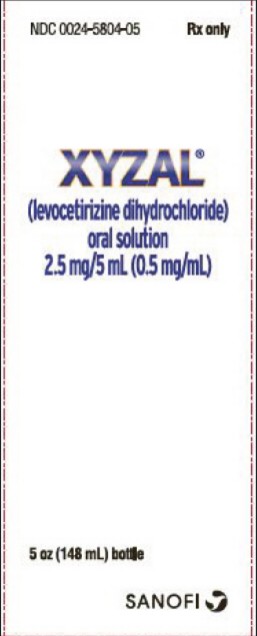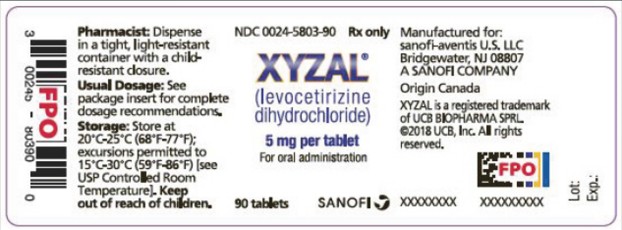 DRUG LABEL: Xyzal
NDC: 41167-5803 | Form: TABLET, FILM COATED
Manufacturer: Chattem, Inc.
Category: prescription | Type: HUMAN PRESCRIPTION DRUG LABEL
Date: 20250722

ACTIVE INGREDIENTS: LEVOCETIRIZINE DIHYDROCHLORIDE 5 mg/1 1
INACTIVE INGREDIENTS: MICROCRYSTALLINE CELLULOSE; LACTOSE MONOHYDRATE; SILICON DIOXIDE; MAGNESIUM STEARATE; HYPROMELLOSE, UNSPECIFIED; TITANIUM DIOXIDE; POLYETHYLENE GLYCOL 400; FD&C RED NO. 40; SHELLAC

HIGHLIGHTS OF PRESCRIBING INFORMATION

These highlights do not include all the information needed to use XYZAL® safely and effectively. See full prescribing information for XYZAL.
XYZAL (levocetirizine dihydrochloride) tablets, for oral use
XYZAL (levocetirizine dihydrochloride) oral solution
Initial U.S. Approval: 1995

RECENT MAJOR CHANGES

Warnings and Precautions, Risk of New Onset Pruritus After Discontinuation of XYZAL (5.3) 07/2025

1 INDICATIONS AND USAGE

XYZAL is a histamine H1-receptor antagonist indicated for:

- The relief of symptoms associated with perennial allergic rhinitis (1.1)
- The treatment of the uncomplicated skin manifestations of chronic idiopathic urticaria (1.2)

2 DOSAGE AND ADMINISTRATION

Perennial Allergic Rhinitis (2.1)

- Children 6 months to 2 years of age: 1.25 mg (1/2 teaspoon oral solution) (2.5 mL) once daily in the evening

Chronic Idiopathic Urticaria (2.2)

- Adults and children 12 years of age and older: 5 mg once daily in the evening
- Children 6 to 11 years of age: 2.5 mg once daily in the evening
- Children 6 months to 5 years of age: 1.25 mg (1/2 teaspoon oral solution) (2.5 mL) once daily in the evening
- Renal Impairment
  Adjust the dose in patients 12 years of age and older with decreased renal function (12.3)

3 DOSAGE FORMS AND STRENGTHS

- Immediate release breakable (scored) tablets, 5 mg (3)
- Immediate release oral solution, 2.5 mg per 5 mL (0.5 mg per mL) (3)

4 CONTRAINDICATIONS

- Patients with a known hypersensitivity to levocetirizine or any of the ingredients of XYZAL or to cetirizine (4.1)
- Patients with end-stage renal disease at less than 10 mL/min creatinine clearance or patients undergoing hemodialysis (4.2)
- Children 6 months to 11 years of age with renal impairment (4.3)

5 WARNINGS AND PRECAUTIONS

- Somnolence: Somnolence, fatigue, and asthenia have been reported with use of XYZAL in some patients in clinical trials. Avoid engaging in hazardous occupations requiring complete mental alertness such as driving or operating machinery when taking XYZAL. Avoid concurrent use of alcohol or other central nervous system depressants with XYZAL. (5.1)
- Urinary Retention: Urinary retention has been reported with use of XYZAL. Use with caution in patients with predisposing factors of urinary retention (e.g. spinal cord lesion, prostatic hyperplasia). Discontinue XYZAL if urinary retention occurs. (5.2)
- Risk of New Onset Pruritus After Discontinuation of XYZAL: New onset pruritus within a few days after discontinuation of XYZAL has been reported, usually after long-term use (e.g., few months to years) of XYZAL. Symptoms may improve with restarting or tapering XYZAL (5.3).

6 ADVERSE REACTIONS

The most common adverse reactions (rate ≥2% and > placebo) were somnolence, nasopharyngitis, fatigue, dry mouth, and pharyngitis in subjects 12 years of age and older, and pyrexia, somnolence, cough, and epistaxis in children 6 to 12 years of age. In subjects 1 to 5 years of age, the most common adverse reactions (rate ≥2% and > placebo) were pyrexia, diarrhea, vomiting, and otitis media. In subjects 6 to 11 months of age, the most common adverse reactions (rate ≥3% and > placebo) were diarrhea and constipation. (6.1).

To report SUSPECTED ADVERSE REACTIONS, contact sanofi-aventis U.S. LLC at 1-800-633-1610 or FDA at 1-800-FDA-1088 or www.fda.gov/medwatch.

8 USE IN SPECIFIC POPULATIONS

- Renal Impairment
  Because XYZAL is substantially excreted by the kidneys, the risk of adverse reactions to this drug may be greater in patients with impaired renal function. (8.6, 12.3)
- Pediatric Use
  Do not exceed the recommended doses of 2.5 mg and 1.25 mg once daily in children 6 to 11 years and 6 months to 5 years of age, respectively. Systemic exposure with these doses in respective pediatric age groups is comparable to that from a 5 mg once daily dose in adults. (12.3)

FULL PRESCRIBING INFORMATION

1 INDICATIONS AND USAGE

1.1 Perennial Allergic Rhinitis

XYZAL is indicated for the relief of symptoms associated with perennial allergic rhinitis in children 6 months to 2 years of age.

1.2 Chronic Idiopathic Urticaria

XYZAL is indicated for the treatment of the uncomplicated skin manifestations of chronic idiopathic urticaria in adults and children 6 months of age and older.

2 DOSAGE AND ADMINISTRATION

XYZAL is available as 2.5 mg/5 mL (0.5 mg/mL) oral solution and as 5 mg breakable (scored) tablets, allowing for the administration of 2.5 mg, if needed. XYZAL can be taken without regard to food consumption.

2.1 Perennial Allergic Rhinitis

Children 6 months to 2 Years of Age

The recommended initial dose of XYZAL is 1.25 mg (1/2 teaspoon oral solution) (2.5 mL) once daily in the evening. The 1.25 mg once daily dose should not be exceeded based on comparable exposure to adults receiving 5 mg [see Clinical Pharmacology (12.3)].

2.2 Chronic Idiopathic Urticaria

Adults and Children 12 Years of Age and Older

The recommended dose of XYZAL is 5 mg (1 tablet or 2 teaspoons [10 mL] oral solution) once daily in the evening. Some patients may be adequately controlled by 2.5 mg (1/2 tablet or 1 teaspoon [5 mL] oral solution) once daily in the evening.

Children 6 to 11 Years of Age

The recommended dose of XYZAL is 2.5 mg (1/2 tablet or 1 teaspoon [5 mL] oral solution) once daily in the evening. The 2.5 mg dose should not be exceeded because the systemic exposure with 5 mg is approximately twice that of adults [see Clinical Pharmacology (12.3)].

Children 6 months to 5 Years of Age

The recommended initial dose of XYZAL is 1.25 mg (1/2 teaspoon oral solution) (2.5 mL) once daily in the evening. The 1.25 mg once daily dose should not be exceeded based on comparable exposure to adults receiving 5 mg [see Clinical Pharmacology (12.3)].

Dose Adjustment for Renal and Hepatic Impairment

In adults and children 12 years of age and older with:

- Mild renal impairment (creatinine clearance [CLCR] = 50-80 mL/min): a dose of 2.5 mg once daily is recommended;
- Moderate renal impairment (CLCR = 30-50 mL/min): a dose of 2.5 mg once every other day is recommended;
- Severe renal impairment (CLCR = 10-30 mL/min): a dose of 2.5 mg twice weekly (administered once every 3-4 days) is recommended;
- End-stage renal disease patients (CLCR <10 mL/min) and patients undergoing hemodialysis should not receive XYZAL.

No dose adjustment is needed in patients with solely hepatic impairment. In patients with both hepatic impairment and renal impairment, adjustment of the dose is recommended.

3 DOSAGE FORMS AND STRENGTHS

XYZAL oral solution is a clear, colorless liquid containing 0.5 mg of levocetirizine dihydrochloride per mL.

XYZAL tablets are white, film-coated, oval-shaped, scored, imprinted (with the letter Y in red color on both halves of the scored tablet) and contain 5 mg levocetirizine dihydrochloride.

4 CONTRAINDICATIONS

The use of XYZAL is contraindicated in:

4.1 Patients with Known Hypersensitivity

Patients with known hypersensitivity to levocetirizine or any of the ingredients of XYZAL, or to cetirizine. Observed reactions range from urticaria to anaphylaxis [see Adverse Reactions (6.2)].

4.2 Patients with End-Stage Renal Disease

Patients with end-stage renal disease (CLCR <10 mL/min) and patients undergoing hemodialysis

4.3 Pediatric Patients with Impaired Renal Function

Children 6 months to 11 years of age with impaired renal function

5 WARNINGS AND PRECAUTIONS

5.1 Somnolence

In clinical trials the occurrence of somnolence, fatigue, and asthenia has been reported in some patients under therapy with XYZAL. Patients should be cautioned against engaging in hazardous occupations requiring complete mental alertness, and motor coordination such as operating machinery or driving a motor vehicle after ingestion of XYZAL. Concurrent use of XYZAL with alcohol or other central nervous system depressants should be avoided because additional reductions in alertness and additional impairment of central nervous system performance may occur.

5.2 Urinary Retention

Urinary retention has been reported post marketing with XYZAL. XYZAL should be used with caution in patients with predisposing factors of urinary retention (e.g. spinal cord lesion, prostatic hyperplasia) as XYZAL may increase the risk of urinary retention. Discontinue XYZAL if urinary retention occurs.

5.3 Risk of New Onset Pruritus After Discontinuation of XYZAL

Cases of pruritus after discontinuation of XYZAL have been reported in the postmarketing setting in patients where pruritus was not present before initiation of XYZAL. Pruritus occurred within a few days of discontinuing XYZAL among patients who used XYZAL long-term (e.g., few months to years). Reported cases of pruritus were infrequent, but some were serious with patients experiencing widespread severe pruritus [See Adverse Reactions (6.2)]. If pruritus occurs after discontinuation of XYZAL, symptoms may improve with restarting or tapering XYZAL.

6 ADVERSE REACTIONS

The following clinically significant adverse reactions are described elsewhere in the labeling:

- Somnolence [see Warnings and Precautions (5.1)]
- Urinary Retention [see Warnings and Precautions (5.2)]
- Risk of New Onset Pruritus After Discontinuation of XYZAL [see Warnings and Precautions (5.3)]

6.1 Clinical Trials Experience

Because clinical trials are conducted under widely varying conditions, adverse reaction rates observed in the clinical trials of a drug cannot be directly compared to rates in the clinical trials of another drug and may not reflect the rates observed in practice.

The safety data described below reflect exposure to XYZAL in 2708 patients with allergic rhinitis or chronic idiopathic urticaria in 14 controlled clinical trials of 1 week to 6 months duration.

The short-term (exposure up to 6 weeks) safety data for adults and adolescents are based upon eight clinical trials in which 1896 patients (825 males and 1071 females aged 12 years and older) were treated with XYZAL 2.5, 5, or 10 mg once daily in the evening.

The short-term safety data from pediatric patients are based upon two clinical trials in which 243 children with allergic rhinitis (162 males and 81 females 6 to 12 years of age) were treated with XYZAL 5 mg once daily for 4 to 6 weeks, one clinical trial in which 114 children (65 males and 49 females 1 to 5 years of age) with allergic rhinitis or chronic idiopathic urticaria were treated with XYZAL 1.25 mg twice daily for 2 weeks, and one clinical trial in which 45 children (28 males and 17 females 6 to 11 months of age) with symptoms of allergic rhinitis or chronic urticaria were treated with XYZAL 1.25 mg once daily for 2 weeks.

The long-term (exposure of 4 or 6 months) safety data in adults and adolescents are based upon two clinical trials in which 428 patients (190 males and 238 females) with allergic rhinitis were exposed to treatment with XYZAL 5 mg once daily. Long term safety data are also available from an 18-month trial in 255 XYZAL-treated subjects 12-24 months of age.

Because clinical trials are conducted under widely varying conditions, adverse reaction rates observed in the clinical trials of a drug cannot be directly compared to rates in the clinical trial of another drug and may not reflect the rates observed in practice.

Adults and Adolescents 12 years of Age and Older

In studies up to 6 weeks in duration, the mean age of the adult and adolescent patients was 32 years, 44% of the patients were men and 56% were women, and the large majority (more than 90%) was Caucasian.

In these trials 43% and 42% of the subjects in the XYZAL 2.5 mg and 5 mg groups, respectively, had at least one adverse event compared to 43% in the placebo group.

In placebo-controlled trials of 1-6 weeks in duration, the most common adverse reactions were somnolence, nasopharyngitis, fatigue, dry mouth, and pharyngitis, and most were mild to moderate in intensity. Somnolence with XYZAL showed dose ordering between tested doses of 2.5, 5 and 10 mg and was the most common adverse reaction leading to discontinuation (0.5%).

Table 1 lists adverse reactions that were reported in greater than or equal to 2% of subjects aged 12 years and older exposed to XYZAL 2.5 mg or 5 mg in eight placebo-controlled clinical trials and that were more common with XYZAL than placebo.

Table 1: Adverse Reactions Reported in ≥2%* of Subjects Aged 12 Years and Older Exposed to XYZAL 2.5 mg or 5 mg Once Daily in Placebo-Controlled Clinical Trials 1-6 Weeks in Duration
Adverse Reactions | XYZAL 2.5 mg (n = 421) | XYZAL 5 mg (n = 1070) | Placebo (n = 912)
Somnolence | 22 (5%) | 61 (6%) | 16 (2%)
Nasopharyngitis | 25 (6%) | 40 (4%) | 28 (3%)
Fatigue | 5 (1%) | 46 (4%) | 20 (2%)
Dry Mouth | 12 (3%) | 26 (2%) | 11 (1%)
Pharyngitis | 10 (2%) | 12 (1%) | 9 (1%)

* Rounded to the closest unit percentage

Additional adverse reactions of medical significance observed at a higher incidence than in placebo in adults and adolescents aged 12 years and older exposed to XYZAL are syncope (0.2%) and weight increased (0.5%).

Pediatric Patients 6 to 12 Years of Age

A total of 243 pediatric patients 6 to 12 years of age received XYZAL 5 mg once daily in two short-term placebo controlled double-blind trials. The mean age of the patients was 9.8 years, 79 (32%) were 6 to 8 years of age, and 50% were Caucasian. Table 2 lists adverse reactions that were reported in greater than or equal to 2% of subjects aged 6 to 12 years exposed to XYZAL 5 mg in placebo-controlled clinical trials and that were more common with XYZAL than placebo.

Table 2: Adverse Reactions Reported in ≥2%* of Subjects Aged 6-12 Years Exposed to XYZAL 5 mg Once Daily in Placebo-Controlled Clinical Trials 4 and 6 Weeks in Duration
Adverse Reactions | XYZAL 5 mg (n = 243) | Placebo (n = 240)
Pyrexia | 10 (4%) | 5 (2%)
Cough | 8 (3%) | 2 (<1%)
Somnolence | 7 (3%) | 1 (<1%)
Epistaxis | 6 (2%) | 1 (<1%)

* Rounded to the closest unit percentage

Pediatric Patients 1 to 5 Years of Age

A total of 114 pediatric patients 1 to 5 years of age received XYZAL 1.25 mg twice daily in a two week placebo-controlled double-blind safety trial. The mean age of the patients was 3.8 years, 32% were 1 to 2 years of age, 71% were Caucasian and 18% were Black. Table 3 lists adverse reactions that were reported in greater than or equal to 2% of subjects aged 1 to 5 years exposed to XYZAL 1.25 mg twice daily in the placebo-controlled safety trial and that were more common with XYZAL than placebo.

Table 3: Adverse Reactions Reported in ≥2%* of Subjects Aged 1-5 Years Exposed to XYZAL 1.25 mg Twice Daily in a 2-Week Placebo-Controlled Clinical Trial
Adverse Reactions | XYZAL 1.25 mg Twice Daily (n = 114) | Placebo (n = 59)
Pyrexia | 5 (4%) | 1 (2%)
Diarrhea | 4 (4%) | 2 (3%)
Vomiting | 4 (4%) | 2 (3%)
Otitis Media | 3 (3%) | 0 (0%)

* Rounded to the closest unit percentage

Pediatric Patients 6 to 11 Months of Age

A total of 45 pediatric patients 6 to 11 months of age received XYZAL 1.25 mg once daily in a two week placebo-controlled double-blind safety trial. The mean age of the patients was 9 months, 51% were Caucasian and 31% were Black. Adverse reactions that were reported in more than 1 subject (i.e. greater than or equal to 3% of subjects) aged 6 to 11 months exposed to XYZAL 1.25 mg once daily in the placebo-controlled safety trial and that were more common with XYZAL than placebo included diarrhea and constipation which were reported in 6 (13%) and 1 (4%) and 3 (7%) and 1 (4%) children in the XYZAL and placebo-treated groups, respectively.

Long-Term Clinical Trials Experience

In two controlled clinical trials, 428 patients (190 males and 238 females) aged 12 years and older were treated with XYZAL 5 mg once daily for 4 or 6 months. The patient characteristics and the safety profile were similar to that seen in the short-term studies. Ten (2.3%) patients treated with XYZAL discontinued because of somnolence, fatigue or asthenia compared to 2 (<1%) in the placebo group.

There are no long term clinical trials in children below 12 years of age with allergic rhinitis or chronic idiopathic urticaria.

Laboratory Test Abnormalities

Elevations of blood bilirubin and transaminases were reported in <1% of patients in the clinical trials. The elevations were transient and did not lead to discontinuation in any patient.

6.2 Postmarketing Experience

In addition to the adverse reactions reported during clinical trials and listed above, the following adverse reactions have also been identified during postapproval use of XYZAL. Because these reactions are reported voluntarily from a population of uncertain size, it is not always possible to reliably estimate their frequency or establish a causal relationship to drug exposure.

- Cardiac disorders: palpitations, tachycardia
- Ear and labyrinth disorders: vertigo
- Eye disorders: blurred vision, visual disturbances
- Gastrointestinal disorders: nausea, vomiting
- General disorders and administration site conditions: edema
- Hepatobiliary disorders: hepatitis
- Immune system disorders: anaphylaxis and hypersensitivity
- Metabolism and nutrition disorders: increased appetite
- Musculoskeletal, connective tissues, and bone disorders: arthralgia, myalgia
- Nervous system disorders: dizziness, dysgeusia, febrile seizure, movement disorders (including dystonia and oculogyric crisis), paresthesia, seizure (reported in subjects with and without a known seizure disorder), tremor
- Psychiatric disorders: aggression and agitation, depression, hallucinations, insomnia, nightmare, suicidal ideation
- Renal and urinary disorders: dysuria, urinary retention
- Respiratory, thoracic, and mediastinal disorders: dyspnea
- Skin and subcutaneous tissue disorders: angioedema, fixed drug eruption, pruritus, rash, urticaria, and new onset pruritus within a few days after discontinuation of XYZAL, usually after long-term use (e.g., few months to years) of XYZAL

Besides these reactions reported under treatment with XYZAL, other potentially severe adverse reactions have been reported from the postmarketing experience with cetirizine. Since levocetirizine is the principal pharmacologically active component of cetirizine, one should take into account the fact that the following adverse reactions could also potentially occur under treatment with XYZAL.

- Cardiac disorders: severe hypotension
- Gastrointestinal disorders: cholestasis
- Nervous system disorders: extrapyramidal symptoms, myoclonus, orofacial dyskinesia, tic
- Pregnancy, puerperium and perinatal conditions: stillbirth
- Renal and urinary disorders: glomerulonephritis
- Skin and subcutaneous tissue disorders: acute generalized exanthematous pustulosis (AGEP)

7 DRUG INTERACTIONS

In vitro data indicate that levocetirizine is unlikely to produce pharmacokinetic interactions through inhibition or induction of liver drug-metabolizing enzymes. No in vivo drug-drug interaction studies have been performed with levocetirizine. Drug interaction studies have been performed with racemic cetirizine.

7.1 Antipyrine, Azithromycin, Cimetidine, Erythromycin, Ketoconazole, Theophylline, and Pseudoephedrine

Pharmacokinetic interaction studies performed with racemic cetirizine demonstrated that cetirizine did not interact with antipyrine, pseudoephedrine, erythromycin, azithromycin, ketoconazole, and cimetidine. There was a small decrease (~16%) in the clearance of cetirizine caused by a 400 mg dose of theophylline. It is possible that higher theophylline doses could have a greater effect.

7.2 Ritonavir

Ritonavir increased the plasma AUC of cetirizine by about 42% accompanied by an increase in half-life (53%) and a decrease in clearance (29%) of cetirizine. The disposition of ritonavir was not altered by concomitant cetirizine administration.

8 USE IN SPECIFIC POPULATIONS

8.1 Pregnancy

Risk Summary

Available data from published literature and postmarketing experience with levocetirizine use in pregnant women are insufficient to identify any drug-associated risks of miscarriage, birth defects, or adverse maternal or fetal outcomes. In animal reproduction studies, there was no evidence of fetal harm with administration of levocetirizine by the oral route to pregnant rats and rabbits, during the period of organogenesis, at doses up to 390 times and 470 times, respectively, the maximum recommended human dose (MRHD) in adults. In rats treated during late gestation and the lactation period, cetirizine had no effects on pup development at oral doses up to approximately 60 times the MRHD in adults. In mice treated during late gestation and the lactation period, cetirizine administered by the oral route to the dams had no effects on pup development at a dose that was approximately 25 times the MRHD in adults; however, lower pup weight gain during lactation was observed at a dose that was 95 times the MRHD in adults [see Data].

The estimated background risk of major birth defects and miscarriage for the indicated population is unknown. All pregnancies have a background risk of birth defect, loss, or other adverse outcomes. In the U.S. general population, the estimated background risks of major birth defects and miscarriage in clinically recognized pregnancies is 2% to 4% and 15% to 20%, respectively.

Data

Animal data

In embryo-fetal development studies, pregnant rats received daily doses of levocetirizine up to 200 mg/kg/day from gestation days 6 to 15 and pregnant rabbits received daily doses of levocetirizine up to 120 mg/kg/day from gestation days 6 to 18. Levocetirizine produced no evidence of fetal harm in rats and rabbits at doses up to 390 and 470 times the MRHD, respectively (on a mg/m^2 basis with maternal oral doses of 200 and 120 mg/kg/day in rats and rabbits, respectively).

No prenatal and postnatal development (PPND) studies in animals have been conducted with levocetirizine. In a PPND study conducted in mice, cetirizine was administered at oral doses up to 96 mg/kg/day from gestation day 15 through lactation day 21. Cetirizine lowered pup body weight gain during lactation at an oral dose in dams that was approximately 95 times the MRHD (on a mg/m^2 basis with a maternal oral dose of 96 mg/kg/day); however, there were no effects on pup weight gain at an oral dose in dams that was approximately 25 times the MRHD (on a mg/m^2 basis with a maternal oral dose of 24 mg/kg/day). In a PPND study conducted in rats, cetirizine was administered at oral doses up to 180 mg/kg/day from gestation day 17 to lactation day 22. Cetirizine did not have any adverse effects on rat dams or offspring development at doses up to approximately 60 times the MRHD (on a mg/m^2 basis with a maternal oral dose of 30 mg/kg/day). Cetirizine caused excessive maternal toxicity at an oral dose in dams that was approximately 350 times the MRHD (on a mg/m^2 basis with a maternal oral dose of 180 mg/kg/day).

8.2 Lactation

Risk Summary

There are no data on the presence of levocetirizine in human milk, the effects on the breastfed infant, or the effects on milk production. However, cetirizine has been reported to be present in human breast milk. In mice and beagle dogs, studies indicated that cetirizine was excreted in milk [see Data]. When a drug is present in animal milk, it is likely the drug will be present in human milk. The developmental and health benefits of breastfeeding should be considered along with the mother’s clinical need for XYZAL and any potential adverse effects on the breastfed child from XYZAL or from the underlying maternal condition.

Data

Animal data

Cetirizine was detected in the milk of mice. No adverse developmental effects on pups were seen when cetirizine was administered orally to dams during lactation at a dose that was approximately 25 times the MRHD in adults [see Use in Specific Populations (8.1)]. Studies in beagle dogs indicated that approximately 3% of the dose of cetirizine was excreted in milk. The concentration of drug in animal milk does not necessarily predict the concentration of drug in human milk.

8.4 Pediatric Use

The recommended dose of XYZAL for the treatment of the uncomplicated skin manifestations of chronic idiopathic urticaria in patients 6 months to 17 years of age is based on extrapolation of efficacy from adults 18 years of age and older [see Clinical Studies (14)].

The recommended dose of XYZAL in patients 6 months to 2 years of age for the treatment of the symptoms of perennial allergic rhinitis and 6 months to 11 years of age with chronic idiopathic urticaria is based on cross-study comparisons of the systemic exposure of XYZAL in adults and pediatric patients and on the safety profile of XYZAL in both adult and pediatric patients at doses equal to or higher than the recommended dose for patients 6 months to 11 years of age.

The safety of XYZAL 5 mg once daily was evaluated in 243 pediatric patients 6 to 12 years of age in two placebo-controlled clinical trials lasting 4 and 6 weeks. The safety of XYZAL 1.25 mg twice daily was evaluated in one 2-week clinical trial in 114 pediatric patients 1 to 5 years of age and the safety of XYZAL 1.25 mg once daily was evaluated in one 2-week clinical trial in 45 pediatric patients 6 to 11 months of age [see Adverse Reactions (6.1)].

The effectiveness of XYZAL 1.25 mg once daily (6 months to 5 years of age) and 2.5 mg once daily (6 to 11 years of age) for the treatment of the symptoms of perennial allergic rhinitis and chronic idiopathic urticaria is supported by the extrapolation of demonstrated efficacy of XYZAL 5 mg once daily in patients 12 years of age and older based on the pharmacokinetic comparison between adults and children.

Cross-study comparisons indicate that administration of a 5 mg dose of XYZAL to 6 to 12 year old pediatric patients resulted in about 2-fold the systemic exposure (AUC) observed when 5 mg of XYZAL was administered to healthy adults. Therefore, in children 6 to 11 years of age the recommended dose of 2.5 mg once daily should not be exceeded. In a population pharmacokinetics study the administration of 1.25 mg once daily in children 6 months to 5 years of age resulted in systemic exposure comparable to 5 mg once daily in adults. [see Dosage and Administration (2.2), Clinical Studies (14), and Clinical Pharmacology (12.3)].

8.5 Geriatric Use

Clinical studies of XYZAL for each approved indication did not include sufficient numbers of patients aged 65 years and older to determine whether they respond differently than younger patients. Other reported clinical experience has not identified differences in responses between the elderly and younger patients. In general, dose selection for an elderly patient should be cautious, usually starting at the low end of the dosing range reflecting the greater frequency of decreased hepatic, renal, or cardiac function and of concomitant disease or other drug therapy.

8.6 Renal Impairment

XYZAL is known to be substantially excreted by the kidneys and the risk of adverse reactions to this drug may be greater in patients with impaired renal function. Because elderly patients are more likely to have decreased renal function, care should be taken in dose selection and it may be useful to monitor renal function [see Dosage and Administration (2) and Clinical Pharmacology (12.3)].

8.7 Hepatic Impairment

As levocetirizine is mainly excreted unchanged by the kidneys, it is unlikely that the clearance of levocetirizine is significantly decreased in patients with solely hepatic impairment [see Clinical Pharmacology (12.3)].

10 OVERDOSAGE

Overdosage has been reported with XYZAL.

Symptoms of overdose may include drowsiness in adults. In children agitation and restlessness may initially occur, followed by drowsiness. There is no known specific antidote to XYZAL. Should overdose occur, symptomatic or supportive treatment is recommended. XYZAL is not effectively removed by dialysis, and dialysis will be ineffective unless a dialyzable agent has been concomitantly ingested.

The acute maximal non-lethal oral dose of levocetirizine was 240 mg/kg in mice (approximately 190 times the maximum recommended daily oral dose in adults, approximately 230 times the maximum recommended daily oral dose in children 6 to 11 years of age, and approximately 180 times the maximum recommended daily oral dose in children 6 months to 5 years of age on a mg/m^2 basis). In rats the maximal non-lethal oral dose was 240 mg/kg (approximately 390 times the maximum recommended daily oral dose in adults, approximately 460 times the maximum recommended daily oral dose in children 6 to 11 years of age, and approximately 370 times the maximum recommended daily oral dose in children 6 months to 5 years of age on a mg/m^2 basis).

11 DESCRIPTION

Levocetirizine dihydrochloride, the active component of XYZAL tablets and oral solution, is an orally active H1-receptor antagonist. The chemical name is (R)-[2-[4-[(4-chlorophenyl) phenylmethyl]-1-piperazinyl] ethoxy] acetic acid dihydrochloride. Levocetirizine dihydrochloride is the R enantiomer of cetirizine hydrochloride, a racemic compound with antihistaminic properties. The empirical formula of levocetirizine dihydrochloride is C21H25ClN2O3•2HCl. The molecular weight is 461.82 and the chemical structure is shown below:

Levocetirizine dihydrochloride is a white, crystalline powder and is water soluble.

XYZAL 5 mg tablets are formulated as immediate release, white, film-coated, oval-shaped scored tablets for oral administration. The tablets are imprinted on both halves of the scored line with the letter Y in red (Opacode® Red). Inactive ingredients are: microcrystalline cellulose, lactose monohydrate, colloidal anhydrous silica, and magnesium stearate. The film coating contains hypromellose, titanium dioxide, and macrogol 400.

XYZAL 0.5 mg/mL oral solution is formulated as an immediate release, clear, colorless liquid. Inactive ingredients are: sodium acetate trihydrate, glacial acetic acid, maltitol solution, glycerin, methylparaben, propylparaben, saccharin, flavoring (consisting of triacetin, natural & artificial flavors, dl-alpha-tocopherol), purified water.

12 CLINICAL PHARMACOLOGY

12.1 Mechanism of Action

Levocetirizine, the active enantiomer of cetirizine, is an antihistamine; its principal effects are mediated via selective inhibition of H1 receptors. The antihistaminic activity of levocetirizine has been documented in a variety of animal and human models. In vitro binding studies revealed that levocetirizine has an affinity for the human H1-receptor 2-fold higher than that of cetirizine (Ki = 3 nmol/L vs. 6 nmol/L, respectively). The clinical relevance of this finding is unknown.

12.2 Pharmacodynamics

Studies in adult healthy subjects showed that levocetirizine at doses of 2.5 mg and 5 mg inhibited the skin wheal and flare caused by the intradermal injection of histamine. In contrast, dextrocetirizine exhibited no clear change in the inhibition of the wheal and flare reaction. Levocetirizine at a dose of 5 mg inhibited the wheal and flare caused by intradermal injection of histamine in 14 pediatric subjects (aged 6 to 11 years) and the activity persisted for at least 24 hours. The clinical relevance of histamine wheal skin testing is unknown.

A QT/QTc study using a single dose of 30 mg of levocetirizine did not demonstrate an effect on the QTc interval. While a single dose of levocetirizine had no effect, the effects of levocetirizine may not be at steady state following single dose. The effect of levocetirizine on the QTc interval following multiple dose administration is unknown. Levocetirizine is not expected to have QT/QTc effects because of the results of QTc studies with cetirizine and the long postmarketing history of cetirizine without reports of QT prolongation.

12.3 Pharmacokinetics

Levocetirizine exhibited linear pharmacokinetics over the therapeutic dose range in adult healthy subjects.

Absorption

Levocetirizine is rapidly and extensively absorbed following oral administration. In adults, peak plasma concentrations are achieved 0.9 hour after administration of the oral tablet. The accumulation ratio following daily oral administration is 1.12 with steady state achieved after 2 days. Peak concentrations are typically 270 ng/mL and 308 ng/mL following a single and a repeated 5 mg once daily dose, respectively. Food had no effect on the extent of exposure (AUC) of the levocetirizine tablet, but Tmax was delayed by about 1.25 hours and Cmax was decreased by about 36% after administration with a high fat meal; therefore, levocetirizine can be administered with or without food.

A dose of 5 mg (10 mL) of XYZAL oral solution is bioequivalent to a 5 mg dose of XYZAL tablets. Following oral administration of a 5 mg dose of XYZAL oral solution to healthy adult subjects, the mean peak plasma concentrations were achieved approximately 0.5 hour post dose.

Distribution

The mean plasma protein binding of levocetirizine in vitro ranged from 91 to 92%, independent of concentration in the range of 90-5000 ng/mL, which includes the therapeutic plasma levels observed. Following oral dosing, the average apparent volume of distribution is approximately 0.4 L/kg, representative of distribution in total body water.

Metabolism

The extent of metabolism of levocetirizine in humans is less than 14% of the dose and therefore differences resulting from genetic polymorphism or concomitant intake of hepatic drug metabolizing enzyme inhibitors are expected to be negligible. Metabolic pathways include aromatic oxidation, N- and O-dealkylation, and taurine conjugation. Dealkylation pathways are primarily mediated by CYP3A4 while aromatic oxidation involves multiple and/or unidentified CYP isoforms.

Elimination

The plasma half-life in adult healthy subjects was about 8 to 9 hours after administration of oral tablets and oral solution, and the mean oral total body clearance for levocetirizine was approximately 0.63 mL/kg/min. The major route of excretion of levocetirizine and its metabolites is via urine, accounting for a mean of 85.4% of the dose. Excretion via feces accounts for only 12.9% of the dose. Levocetirizine is excreted both by glomerular filtration and active tubular secretion. Renal clearance of levocetirizine correlates with that of creatinine clearance. In patients with renal impairment the clearance of levocetirizine is reduced [see Dosage and Administration (2.2)].

Drug Interaction Studies

In vitro data on metabolite interaction indicate that levocetirizine is unlikely to produce, or be subject to metabolic interactions. Levocetirizine at concentrations well above Cmax level achieved within the therapeutic dose ranges is not an inhibitor of CYP isoenzymes 1A2, 2C9, 2C19, 2A1, 2D6, 2E1, and 3A4, and is not an inducer of UGT1A or CYP isoenzymes 1A2, 2C9 and 3A4.

No formal in vivo drug interaction studies have been performed with levocetirizine. Studies have been performed with the racemic cetirizine [see Drug Interactions (7)].

Pediatric patients

Data from a pediatric pharmacokinetic study with oral administration of a single dose of 5 mg levocetirizine in 14 children age 6 to 11 years with body weight ranging between 20 and 40 kg show that Cmax and AUC values are about 2-fold greater than that reported in healthy adult subjects in a cross-study comparison. The mean Cmax was 450 ng/mL, occurring at a mean time of 1.2 hours, weight-normalized, total body clearance was 30% greater, and the elimination half-life 24% shorter in this pediatric population than in adults.

Dedicated pharmacokinetic studies have not been conducted in pediatric patients younger than 6 years of age. A retrospective population pharmacokinetic analysis was conducted in 323 subjects (181 children 1 to 5 years of age, 18 children 6 to 11 years of age, and 124 adults 18 to 55 years of age) who received single or multiple doses of levocetirizine ranging from 1.25 mg to 30 mg. Data generated from this analysis indicated that administration of 1.25 mg once daily to children 6 months to 5 years of age results in plasma concentrations similar to those of adults receiving 5 mg once daily.

Geriatric patients

Limited pharmacokinetic data are available in elderly subjects. Following once daily repeat oral administration of 30 mg levocetirizine for 6 days in 9 elderly subjects (65-74 years of age), the total body clearance was approximately 33% lower compared to that in younger adults. The disposition of racemic cetirizine has been shown to be dependent on renal function rather than on age. This finding would also be applicable for levocetirizine, as levocetirizine and cetirizine are both predominantly excreted in urine. Therefore, the XYZAL dose should be adjusted in accordance with renal function in elderly patients [see Dosage and Administration (2)].

Gender

Pharmacokinetic results for 77 patients (40 men, 37 women) were evaluated for potential effect of gender. The half-life was slightly shorter in women (7.08 ± 1.72 hr) than in men (8.62 ± 1.84 hr); however, the body weight-adjusted oral clearance in women (0.67 ± 0.16 mL/min/kg) appears to be comparable to that in men (0.59 ± 0.12 mL/min/kg). The same daily doses and dosing intervals are applicable for men and women with normal renal function.

Race

The effect of race on levocetirizine has not been studied. As levocetirizine is primarily renally excreted, and there are no important racial differences in creatinine clearance, pharmacokinetic characteristics of levocetirizine are not expected to be different across races. No race-related differences in the kinetics of racemic cetirizine have been observed.

Renal impairment

Levocetirizine exposure (AUC) exhibited 1.8-, 3.2-, 4.3-, and 5.7-fold increase in mild, moderate, severe, renal impaired, and end-stage renal disease patients, respectively, compared to healthy subjects. The corresponding increases of half-life estimates were 1.4-, 2.0-, 2.9-, and 4-fold, respectively.

The total body clearance of levocetirizine after oral dosing was correlated to the creatinine clearance and was progressively reduced based on severity of renal impairment. Therefore, it is recommended to adjust the dose and dosing intervals of levocetirizine based on creatinine clearance in patients with mild, moderate, or severe renal impairment. In end-stage renal disease patients (CLCR < 10 mL/min) levocetirizine is contraindicated. The amount of levocetirizine removed during a standard 4-hour hemodialysis procedure was <10%.

The dosage of XYZAL should be reduced in patients with mild renal impairment. Both the dosage and frequency of administration should be reduced in patients with moderate or severe renal impairment [see Dosage and Administration (2.2)].

Hepatic impairment

XYZAL has not been studied in patients with hepatic impairment. The non-renal clearance (indicative of hepatic contribution) was found to constitute about 28% of the total body clearance in healthy adult subjects after oral administration.

As levocetirizine is mainly excreted unchanged by the kidney, it is unlikely that the clearance of levocetirizine is significantly decreased in patients with solely hepatic impairment [see Dosage and Administration (2)].

13 NONCLINICAL TOXICOLOGY

13.1 Carcinogenesis, Mutagenesis, Impairment of Fertility

No carcinogenicity studies have been performed with levocetirizine. However, evaluation of cetirizine carcinogenicity studies is relevant for determination of the carcinogenic potential of levocetirizine. In a 2-year carcinogenicity study, in rats, cetirizine was not carcinogenic at dietary doses up to 20 mg/kg (approximately 40, 40, 25, and 10 times the MRHDs in adults, children 6 to 11 years of age, children 2-5 years, and children 6 months to 2 years of age, respectively, on a mg/m^2 basis). In a 2-year carcinogenicity study in mice, cetirizine caused an increased incidence of benign hepatic tumors in males at a dietary dose of 16 mg/kg (approximately 15, 15, 9, and 5 times the MRHDs in adults, children 6 to 11 years of age, children 2-5 years, and children 6 months to 2 years of age, respectively, on a mg/m^2 basis). No increased incidence of benign tumors was observed at a dietary dose of 4 mg/kg (approximately 4, 4, 2, and 1 times the MRHDs in adults, children 6 to 11 years of age, children 2-5 years, and children 6 months to 2 years of age, respectively on a mg/m^2 basis). The clinical significance of these findings during long-term use of XYZAL is not known.

Levocetirizine was not mutagenic in the Ames test, and not clastogenic in the human lymphocyte assay, the mouse lymphoma assay, and in vivo micronucleus test in mice.

Fertility and reproductive performance were unaffected in male and female mice and rats that received cetirizine at oral doses up to 64 and 200 mg/kg/day, respectively (approximately 60 and 390 times the MRHD in adults on a mg/m^2 basis).

14 CLINICAL STUDIES

14.1 Perennial Allergic Rhinitis

Adults and Adolescents 12 Years of Age and Older

The efficacy of XYZAL was evaluated in four randomized, placebo-controlled, double-blind clinical trials in adult and adolescent patients 12 years and older with symptoms of perennial allergic rhinitis. The four clinical trials include two dose-ranging trials of 4 weeks duration and two efficacy trials (one 6-week and one 6-month) in patients with perennial allergic rhinitis.

These trials included a total of 1729 patients (752 males and 977 females) of whom 227 were adolescents 12 to 17 years of age. Efficacy was assessed using a total symptom score from patient recording of 4 symptoms (sneezing, rhinorrhea, nasal pruritus, and ocular pruritus) in three studies and 5 symptoms (sneezing, rhinorrhea, nasal pruritus, ocular pruritus, and nasal congestion) in one study. Patients recorded symptoms using a 0-3 categorical severity scale (0 = absent, 1 = mild, 2 = moderate, 3 = severe) once daily in the evening reflective of the 24 hour treatment period. The primary endpoint was the mean total symptom score averaged over the first week and over 4 weeks for perennial allergic rhinitis trials.

The two dose-ranging trials were conducted to evaluate the efficacy of XYZAL 2.5, 5, and 10 mg once daily in the evening. These trials were 4 weeks in duration and included patients with perennial allergic rhinitis. In these trials, each of the three doses of XYZAL demonstrated greater decrease in the reflective total symptom score than placebo and the difference was statistically significant for all three doses in the two studies. Results for one of these trials are shown in Table 4.

Table 4: Mean Reflective Total Symptom Score* in Allergic Rhinitis Dose-Ranging Trials
Treatment | N | Baseline | On Treatment Adjusted Mean | Difference from Placebo
 |  |  |  | Estimate | 95% CI |  | p-value
Perennial Allergic Rhinitis Trial – Reflective total symptom score
XYZAL 2.5 mg | 133 | 7.14 | 4.12 | 1.17 | (0.71, 1.63) | <0.001
XYZAL 5 mg | 127 | 7.18 | 4.07 | 1.22 | (0.76, 1.69) | <0.001
XYZAL 10 mg | 129 | 7.58 | 4.19 | 1.10 | (0.64, 1.57) | <0.001
Placebo | 128 | 7.22 | 5.29

*Total symptom score is the sum of individual symptoms of sneezing, rhinorrhea, nasal pruritus, and ocular pruritus as assessed by patients on a 0-3 categorical severity scale.

One clinical trial evaluated the efficacy of XYZAL 5 mg once daily in the evening compared to placebo in patients with perennial allergic rhinitis over a 6-week treatment period. Another trial conducted over a 6-month treatment period assessed efficacy at 4 weeks. XYZAL 5 mg demonstrated a greater decrease from baseline in the reflective total symptom score than placebo and the difference from placebo was statistically significant. Results of the former are shown in Table 5.

Table 5: Mean Reflective Total Symptom Score* in Allergic Rhinitis Trials
Treatment | N | Baseline | On Treatment Adjusted Mean | Difference from Placebo
 |  |  |  | Estimate | 95% CI | p-value
Perennial Allergic Rhinitis Trial – Reflective total symptom score
XYZAL 5 mg | 150 | 7.69 | 3.93 | 1.17 | (0.70, 1.64) | <0.001
Placebo | 142 | 7.44 | 5.10

* Total symptom score is the sum of individual symptoms of sneezing, rhinorrhea, nasal pruritus, and ocular pruritus as assessed by patients on a 0-3 categorical severity scale.

Onset of action was evaluated in two environmental exposure unit studies in allergic rhinitis patients with a single dose of XYZAL 2.5 or 5 mg. XYZAL 5 mg was found to have an onset of action 1 hour after oral intake. Onset of action was also assessed from the daily recording of symptoms in the evening before dosing in the allergic rhinitis trials. In these trials, onset of effect was seen after 1 day of dosing.

Pediatric Patients Less than 12 Years of Age

There are no clinical efficacy trials with XYZAL 2.5 mg once daily in pediatric patients under 12 years of age, and no clinical efficacy trials with XYZAL 1.25 mg once daily in pediatric patients 6 months to 5 years of age. The clinical efficacy of XYZAL in pediatric patients under 12 years of age has been extrapolated from adult clinical efficacy trials based on pharmacokinetic comparisons [see Use in Specific Populations (8.4)].

14.2 Chronic Idiopathic Urticaria

Adult Patients 18 Years of Age and Older

The efficacy of XYZAL for the treatment of the uncomplicated skin manifestations of chronic idiopathic urticaria was evaluated in two multi-center, randomized, placebo-controlled, double-blind clinical trials of 4 weeks duration in adult patients 18 to 85 years of age with chronic idiopathic urticaria. The two trials included one 4-week dose-ranging trial and one 4-week single-dose level efficacy trial. These trials included 423 patients (139 males and 284 females). Most patients (>90%) were Caucasian and the mean age was 41. Of these patients, 146 received XYZAL 5 mg once daily in the evening. Efficacy was assessed based on patient recording of pruritus severity on a severity score of 0-3 (0 = none to 3 = severe). The primary efficacy endpoint was the mean reflective pruritus severity score over the first week and over the entire treatment period. Additional efficacy variables were the instantaneous pruritus severity score, the number and size of wheals, and duration of pruritus.

The dose-ranging trial was conducted to evaluate the efficacy of XYZAL 2.5, 5, and 10 mg once daily in the evening. In this trial, each of the three doses of XYZAL demonstrated greater decrease in the reflective pruritus severity score than placebo and the difference was statistically significant for all three doses (see Table 6).

The single dose level trial evaluated the efficacy of XYZAL 5 mg once daily in the evening compared to placebo in patients with chronic idiopathic urticaria over a 4-week treatment period. XYZAL 5 mg demonstrated a greater decrease from baseline in the reflective pruritus severity score than placebo and the difference from placebo was statistically significant.

Duration of pruritus, number and size of wheals, and instantaneous pruritus severity score also showed significant improvement over placebo. The significant improvement in the instantaneous pruritus severity score over placebo confirmed end of dosing interval efficacy (see Table 6).

Table 6: Mean Reflective Pruritus Severity Score in Chronic Idiopathic Urticaria Trials
Treatment | N | Baseline | On Treatment Adjusted Mean | Difference from Placebo
 |  |  |  | Estimate | 95% CI | p-value
Dose-Ranging Trial – Reflective pruritus severity score
XYZAL 2.5 mg | 69 | 2.08 | 1.02 | 0.82 | (0.58, 1.06) | <0.001
XYZAL 5 mg | 62 | 2.07 | 0.92 | 0.91 | (0.66, 1.16) | <0.001
XYZAL 10 mg | 55 | 2.04 | 0.73 | 1.11 | (0.85, 1.37) | <0.001
Placebo | 60 | 2.25 | 1.84
Chronic Idiopathic Urticaria Trial – Reflective pruritus severity score
XYZAL 5 mg | 80 | 2.07 | 0.94 | 0.62 | (0.38, 0.86) | <0.001
Placebo | 82 | 2.06 | 1.56

Pediatric Patients

There are no clinical efficacy trials in pediatric patients with chronic idiopathic urticaria [see Use in Specific Populations (8.4)].

16 HOW SUPPLIED/STORAGE AND HANDLING

XYZAL tablets are white, film-coated, oval-shaped, scored, imprinted (with the letter Y in red color on both halves of the scored tablet) and contain 5 mg levocetirizine dihydrochloride. They are supplied in unit of use HDPE bottles.

90 Tablets (NDC 0024-5803-90)

XYZAL oral solution is a clear, colorless liquid containing 0.5 mg of levocetirizine dihydrochloride per mL.

Oral Solution in 5 oz polypropylene bottles (NDC 0024-5804-05)

Storage

Store at 20ºC to 25ºC (68ºF to 77ºF); excursions permitted to 15ºC to 30ºC (59°F to 86°F) [see USP Controlled Room Temperature].

17 PATIENT COUNSELING INFORMATION

Somnolence

Caution patients against engaging in hazardous occupations requiring complete mental alertness, and motor coordination such as operating machinery or driving a motor vehicle after ingestion of XYZAL [see Warnings and Precautions (5.1)].

Concomitant Use of Alcohol and other Central Nervous System Depressants

Instruct patients to avoid concurrent use of XYZAL with alcohol or other central nervous system depressants because additional reduction in mental alertness may occur [see Warnings and Precautions (5.1)].

Risk of New Onset Pruritus After Discontinuation of XYZAL

Inform patients pruritus has occurred within a few days of discontinuing XYZAL among patients who used XYZAL long-term (e.g., few months to years). Pruritus may improve with restarting or tapering XYZAL [see Warnings and Precautions (5.3)]. Advise patients to seek medical advice if pruritus occurs.

Dosing of XYZAL

Do not exceed the recommended daily dose in adults and adolescents 12 years of age and older of 5 mg once daily in the evening. In children 6 to 11 years of age the recommended dose is 2.5 mg once daily in the evening. In children 6 months to 5 years of age, the recommended dose is 1.25 mg once daily in the evening. Advise patients to not ingest more than the recommended dose of XYZAL because of the increased risk of somnolence at higher doses.

Manufactured for:
sanofi-aventis, U.S. LLC
Bridgewater, NJ 08807
A SANOFI COMPANY

XYZAL is a registered trademark of UCB BIOPHARMA SPRL.

©2025 UCB, Inc. All rights reserved.

PRINCIPAL DISPLAY PANEL

NDC 0024-5804-05
Rx Only
XYZAL
(levocetirizine dihydrochloride)
oral solution
2.5 mg/5 mL (0.5 mg/mL)

PRINCIPAL DISPLAY PANEL

NDC 0024-5803-90
Rx Only
XYZAL
(levocetirizine dihydrochloride)
oral solution
5 mg per tablet
For oral administration